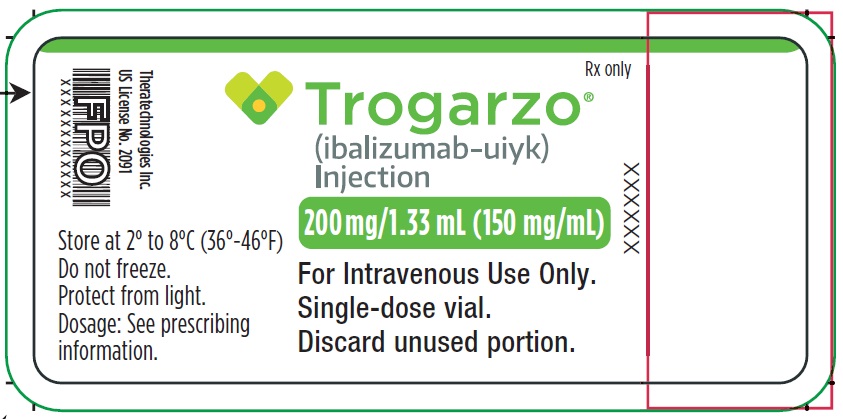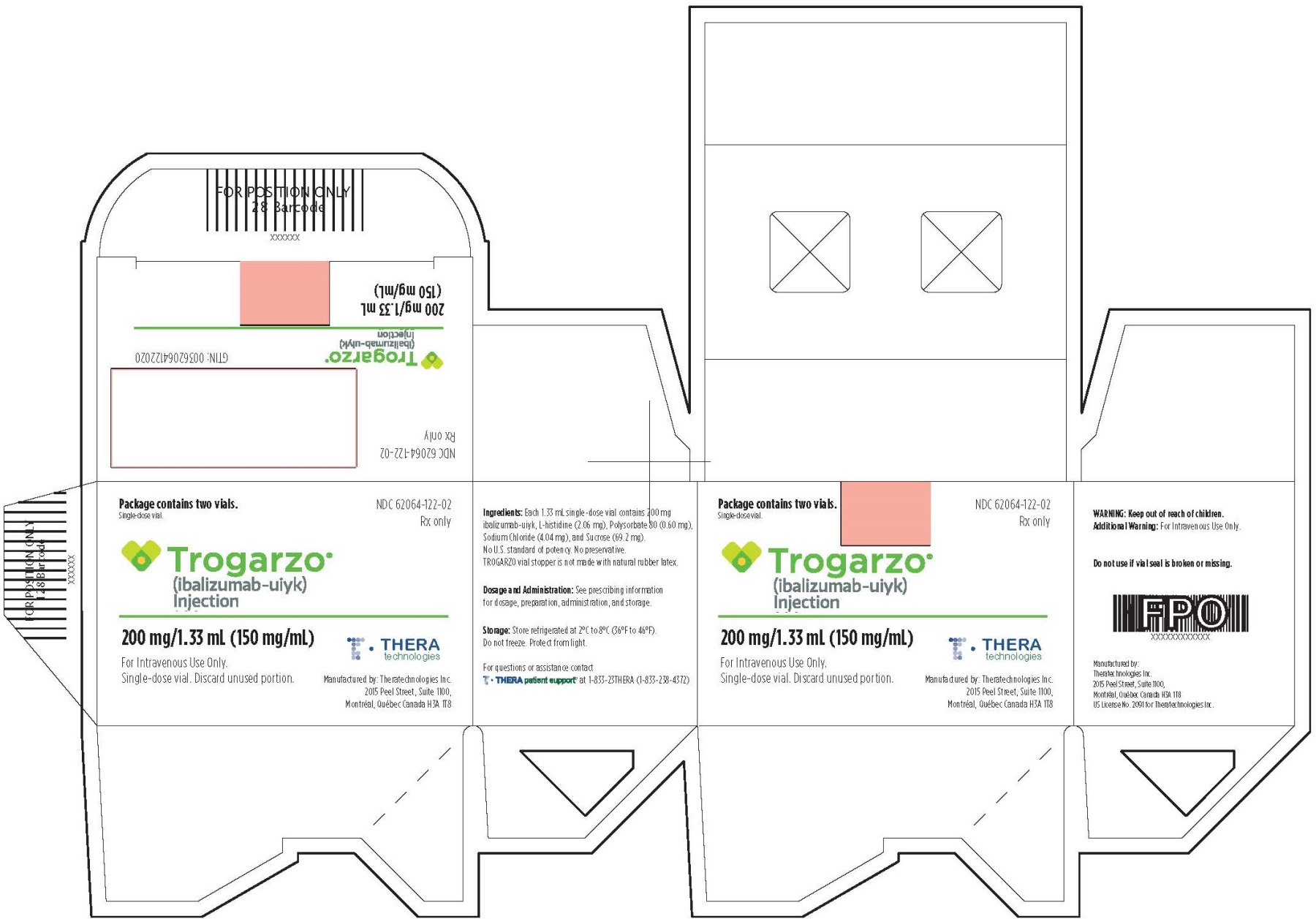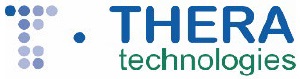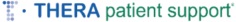 DRUG LABEL: TROGARZO
NDC: 62064-122 | Form: INJECTION, SOLUTION
Manufacturer: Theratechnologies Inc.
Category: prescription | Type: HUMAN PRESCRIPTION DRUG LABEL
Date: 20241230

ACTIVE INGREDIENTS: ibalizumab 150 mg/1 mL
INACTIVE INGREDIENTS: histidine; sucrose; sodium chloride; polysorbate 80; HYDROCHLORIC ACID; water

HIGHLIGHTS OF PRESCRIBING INFORMATION

These highlights do not include all the information needed to use TROGARZO safely and effectively. See full prescribing information for TROGARZO.
TROGARZO® (ibalizumab-uiyk) injection, for intravenous use
Initial U.S. Approval: 2018

1 INDICATIONS AND USAGE

TROGARZO, a CD4-directed post-attachment HIV-1 inhibitor, in combination with other antiretroviral(s), is indicated for the treatment of human immunodeficiency virus type 1 (HIV-1) infection in heavily treatment-experienced adults with multidrug resistant HIV-1 infection failing their current antiretroviral regimen.

RECENT MAJOR CHANGES

Dosage and Administration (2.1, 2.2, 2.3) 12/2023

2 DOSAGE AND ADMINISTRATION

The recommended dosage regimen is a single loading dose of 2,000 mg followed by a maintenance dose of 800 mg every 2 weeks administered as a diluted intravenous infusion (IV infusion) or undiluted intravenous push (IV push). (2.1, 2.2, 2.3)

Duration of IV Infusion or IV Push

 | IV Infusion (Diluted) | IV Push (Undiluted)
Loading Dose 2,000 mg | Over at least 30 minutes | Over at least 90 seconds
Maintenance Dose 800 mg | Over at least 15 minutes | Over at least 30 seconds

3 DOSAGE FORMS AND STRENGTHS

Injection: 200 mg/1.33 mL (150 mg/mL) in a single-dose vial.

4 CONTRAINDICATIONS

Prior hypersensitivity reaction to TROGARZO or any components of the product.

5 WARNINGS AND PRECAUTIONS

- Hypersensitivity reactions including infusion-related reactions and anaphylactic reactions have been reported following infusion of TROGARZO. (5.1)
- Immune Reconstitution Inflammatory Syndrome (IRIS) has been reported in patients treated with combination antiretroviral therapies. (5.2)
- Embryo-Fetal Toxicity: Monitor infants exposed to TROGARZO in utero for signs and symptoms of immunosuppression. (5.3, 8.1)

6 ADVERSE REACTIONS

The most common adverse reactions (incidence ≥ 5%) were diarrhea, dizziness, nausea, and rash. (6.1)

To report SUSPECTED ADVERSE REACTIONS, contact THERA patient support® at 1-833-23THERA (1-833-238-4372) or FDA at 1-800-FDA-1088 or www.fda.gov/medwatch.

8 USE IN SPECIFIC POPULATIONS

Lactation: Women infected with HIV should be instructed not to breastfeed due to the potential for HIV transmission. (8.2)

FULL PRESCRIBING INFORMATION

1 INDICATIONS AND USAGE

TROGARZO, in combination with other antiretroviral(s), is indicated for the treatment of human immunodeficiency virus type 1 (HIV-1) infection in heavily treatment-experienced adults with multidrug resistant HIV-1 infection failing their current antiretroviral regimen.

2 DOSAGE AND ADMINISTRATION

2.1 Recommended Dosage

The recommended dosage regimen is a single loading dose of 2,000 mg followed by a maintenance dose of 800 mg every 2 weeks administered as a diluted intravenous infusion (IV infusion) or undiluted intravenous push (IV push) [see Dosage and Administration (2.2, 2.3)]. TROGARZO is available in a single-dose, 2 mL vial containing 150 mg/mL of ibalizumab-uiyk. Each vial delivers approximately 1.33 mL containing 200 mg of ibalizumab-uiyk. Dose modifications of TROGARZO are not required when administered with any other antiretroviral or any other treatments.

2.2 Preparation

Parenteral drug products should be inspected visually for particulate matter and discoloration prior to administration, whenever solution and container permit. Discard vial if solution is cloudy, if there is pronounced discoloration or if there is foreign particulate matter.

See Table 1 for the appropriate number of vials required to prepare both the loading dose of 2,000 mg and the maintenance doses of 800 mg.

Table 1. Recommended TROGARZO Dose and Number of Vials Per Administration
TROGARZO Dose | TROGARZO Vials (Total Volume to be Withdrawn)
Loading dose of 2,000 mg; (IV infusion or undiluted IV push) | 10 vials (13.3 mL)
Maintenance dose of 800 mg; (IV infusion or undiluted IV push) | 4 vials (5.32 mL)

TROGARZO solution for IV infusion or IV push should be prepared by a trained medical professional using aseptic technique as follows:

For intravenous infusion

For administration as an IV infusion, the appropriate number of vials are diluted in 250 mL of 0.9% Sodium Chloride Injection, USP.

• Remove the flip-off cap from the single-dose vial and wipe the stopper with an alcohol swab.

• Insert sterile syringe needle into the vial through the center of the stopper and withdraw 1.33 mL from each vial (NOTE: a small residual amount may remain in the vial, discard unused portion) and transfer into a 250 mL intravenous bag of 0.9% Sodium Chloride Injection, USP. Other intravenous diluents must not be used to prepare the TROGARZO solution for infusion.

• Once diluted, the TROGARZO solution should be administered immediately.

• If not administered immediately, store the diluted TROGARZO solution at room temperature (20°C to 25°C, 68°F to 77°F) for up to 4 hours, or refrigerated (2°C to 8°C, 36°F to 46°F) for up to 24 hours. If refrigerated, allow the diluted TROGARZO solution to stand at room temperature (20°C to 25°C, 68°F to 77°F) for at least 30 minutes but no more than 4 hours prior to administration.

• Discard partially used vials or empty vials of TROGARZO and any unused portion of the diluted TROGARZO solution.

For intravenous push

For administration as an IV push, undiluted TROGARZO solution is administered.

• Allow the vials to stand at room temperature for approximately 5 minutes.

• Remove the flip-off cap from the single-dose vial and wipe the stopper with an alcohol swab.

• Insert sterile syringe needle into the vial through the center of the stopper and withdraw 1.33 mL from each vial (NOTE: a small residual amount may remain in the vial, discard unused portion).

• The undiluted TROGARZO solution should be administered immediately.

• Discard partially used vials or empty vials of TROGARZO and any unused portion of the undiluted TROGARZO solution.

2.3 Administration

TROGARZO solution should be administered by a trained medical professional.

Administer TROGARZO intravenously (as an IV infusion or IV push) in the cephalic vein of the patients right or left arm. If this vein is not accessible, an appropriate vein located elsewhere can be used. Table 2 outlines the duration of IV infusion or IV push for the loading dose and maintenance dose.

Table 2. Duration of IV Infusion or IV Push
 | IV Infusion (Diluted) | IV Push (Undiluted)
Loading Dose 2,000 mg | Over at least 30 minutes | Over at least 90 seconds
Maintenance Dose 800 mg | Over at least 15 minutes | Over at least 30 seconds

After the IV infusion is complete, flush with 30 mL of 0.9% Sodium Chloride Injection, USP.

After the IV push is complete, flush with 2 to 5 mL of 0.9% Sodium Chloride Injection, USP.

All patients must be observed for 1 hour after completion of TROGARZO loading dose as an IV infusion or IV push. If the patient does not experience an infusion-associated adverse reaction, the post-administration observation time for the subsequent maintenance doses (IV infusion or IV push) can be reduced to 15 minutes.

If a maintenance dose (800 mg) of TROGARZO is missed by 3 days or longer beyond the scheduled dosing day, a loading dose (2,000 mg) should be administered as early as possible. Resume maintenance dosing (800 mg) every 14 days thereafter.

3 DOSAGE FORMS AND STRENGTHS

Injection: 200 mg/1.33 mL (150 mg/mL) colorless to slightly yellow and clear to slightly opalescent solution with no visible particles in a single-dose vial.

4 CONTRAINDICATIONS

TROGARZO is contraindicated in patients with a prior hypersensitivity reaction to TROGARZO or any components of the product [see Warnings and Precautions (5.1)].

5 WARNINGS AND PRECAUTIONS

5.1 Hypersensitivity Including Infusion-Related and Anaphylactic Reactions

Hypersensitivity reactions including infusion-related reactions and anaphylactic reactions have been reported following infusion of TROGARZO during post-approval use. Symptoms may include dyspnea, angioedema, wheezing, chest pain, chest tightness, cough, hot flush, nausea, and vomiting. If signs and symptoms of an anaphylactic or other clinically significant hypersensitivity reaction occur, immediately discontinue administration of TROGARZO and initiate appropriate treatment. The use of TROGARZO is contraindicated in patients with known hypersensitivity with TROGARZO [see Contraindications (4), Adverse Reactions (6.2)].

5.2 Immune Reconstitution Inflammatory Syndrome

Immune reconstitution inflammatory syndrome has been reported in one patient treated with TROGARZO in combination with other antiretrovirals. During the initial phase of combination antiretroviral therapies, patients whose immune systems respond may develop an inflammatory response to indolent or residual opportunistic infections, which may necessitate further evaluation and treatment.

5.3 Embryo-Fetal Toxicity

Based on animal data, TROGARZO may cause reversible immunosuppression (CD4+ T cell and B cell lymphocytopenia) in infants born to mothers exposed to TROGARZO during pregnancy. Immune phenotyping of the peripheral blood and expert consultation are recommended to provide guidance regarding monitoring and management of exposed infants based on the degree of immunosuppression observed. The safety of administering live or live-attenuated vaccines in exposed infants is unknown. [see Use In Specific Populations (8.1)]

6 ADVERSE REACTIONS

The following adverse drug reactions are discussed in other sections of the labeling:

- Immune Reconstitution Inflammatory Syndrome [see Warnings and Precautions (5.2)]

6.1 Clinical Trial Experience

Because clinical trials are conducted under widely varying conditions, adverse reaction rates observed in the clinical trials of a drug cannot be directly compared to rates in the clinical trials of another drug and may not reflect the rates observed in practice.

A total of 350 subjects have been exposed to TROGARZO in the ibalizumab clinical development program, including 45 subjects who received TROGARZO through expanded access programs. A total of 19 subjects received TROGARZO via IV push. The safety profile of TROGARZO administered via IV push (Trial TMB-302) was similar to that seen with IV infusion administration (Trial TMB-301) [see Clinical Pharmacology (12.3)].

Trial TMB-301
The primary safety assessment of TROGARZO is based on 24 weeks of data from Trial TMB-301. TMB-301 was a single-arm trial of TROGARZO which enrolled 40 heavily treatment-experienced subjects with multidrug resistant HIV-1 on a failing HIV treatment regimen. Subjects received a single 2,000 mg IV loading dose of TROGARZO followed seven days later by the initiation of an optimized background regimen (OBR) including at least one agent to which the subject's virus was susceptible. Two weeks after the TROGARZO loading dose, 800 mg of TROGARZO was administered IV. The IV administration of TROGARZO 800 mg was continued every 2 weeks through Week 25.

The most common adverse reactions (all Grades) reported in at least 5% of subjects were diarrhea, dizziness, nausea, and rash. Table 3 shows the frequency of adverse reactions occurring in 5% or more of subjects.

Table 3. Adverse Reactions (All Grades) Reported in ≥ 5% of Subjects Receiving TROGARZO and Optimized Background Regimen for 23 Weeks in Trial TMB-301
 | % Subjects N=40
Diarrhea | 8%
Dizziness | 8%
Nausea | 5%
Rash [Includes pooled terms “rash”, “rash erythematous”, “rash generalized”, “rash macular”, “rash maculopapular”, and “rash papular”] | 5%

Most (90%) of the adverse reactions reported were mild or moderate in severity. Two subjects experienced severe adverse reactions: one subject had a severe rash and one subject developed immune reconstitution inflammatory syndrome manifested as an exacerbation of progressive multifocal leukoencephalopathy.

Laboratory Abnormalities
Table 4 shows the frequency of laboratory abnormalities (≥ Grade 3) in Trial TMB-301.

Table 4. Selected Laboratory Abnormalities (≥ Grade 3) in Trial TMB-301
 | % Subjects; N=40
Bilirubin (≥ 2.6 x ULN) | 5%
Direct Bilirubin (> ULN) | 3%
Creatinine (> 1.8 x ULN or 1.5 x baseline) | 10%
Blood Glucose (> 250 mg/dL) | 3%
Lipase (> 3.0 x ULN) | 5%
Uric Acid (> 12 mg/dL) | 3%
Hemoglobin (< 8.5 g/dL) | 3%
Platelets (< 50,000/mm^3) | 3%
Leukocytes (< 1.5 x 10^9 cells/L) | 5%
Neutrophils (< 0.6 x 10^9 cells/L) | 5%

6.2 Postmarketing Experience

The following adverse reactions have been identified during post‐approval use of TROGARZO. Because these reactions are reported voluntarily from a population of uncertain size, it is not possible to reliably estimate their frequency or establish a causal relationship to drug exposure.

- Immune system disorders: hypersensitivity reactions including infusion-related reactions and anaphylactic reactions have been reported [see Warnings and Precautions (5.1)].
- Skin and subcutaneous tissue disorders: pruritus

8 USE IN SPECIFIC POPULATIONS

8.1 Pregnancy

Pregnancy Exposure Registry

There is a pregnancy exposure registry that monitors pregnancy outcomes in women exposed to antiretrovirals during pregnancy. This registry does not include Trogarzo, but likely includes patients’ concomitant antiretroviral drugs. Healthcare providers are encouraged to register patients by calling the Antiretroviral Pregnancy Registry (APR) at 1–800–258–4263.

Risk Summary

Based on animal data, ibalizumab-uiyk use during pregnancy may cause reversible immunosuppression (CD4+ T cell and B cell lymphocytopenia) in infants exposed to ibalizumab-uiyk in utero. Immunoglobulin G (IgG) antibodies, such as ibalizumab-uiyk, are transported across the placenta in significant amounts, especially near term; therefore, ibalizumab-uiyk has the potential to be transferred from the mother to the developing fetus (see Clinical Considerations). There are no available data on ibalizumab-uiyk use in pregnant women to evaluate for a drug- associated risk of major birth defects, miscarriage or adverse maternal or fetal outcomes. The background risk of major birth defects and miscarriage for the indicated population is unknown. All pregnancies have a background risk of birth defect, loss, or other adverse outcomes. In the U.S. general population, the estimated background risk of major birth defects and miscarriage in clinically recognized pregnancies is 2-4% and 15-20%, respectively.

In a reproductive study in monkeys, reversible decreases in CD4+ T cells and B cells and increases in CD8+ T cells were observed within the first 4 weeks after birth in infants born to pregnant monkeys receiving ibalizumab-uiyk intravenously (see Data). Lymphocyte counts returned to near normal levels by 3 months of age. One infant monkey died from a systemic viral infection that may be related to ibalizumab-uiyk-induced immunosuppression. No malformations or premature births were observed in this study.

Clinical Considerations

Fetal/Neonatal Adverse Reactions

Immunoglobulin G (IgG) antibodies are increasingly transported across the placenta as pregnancy progresses, with the largest amount transferred during the third trimester. Administration of TROGARZO during pregnancy may affect immune responses in the in utero-exposed infant. For infants with perinatal exposure to TROGARZO, immune phenotyping of the peripheral blood, including CD4+ T cell and B cell counts, is recommended. Expert consultation is also recommended to provide guidance on monitoring and management (e.g., need for antibiotic or immunoprophylaxis) of exposed infants based on the degree of immunosuppression observed. The safety of administering live or live-attenuated vaccines in exposed infants is unknown.

Data

Animal Data

In an enhanced pre- and post-natal development (ePPND) study, pregnant cynomolgus monkeys were administered intravenous doses of either vehicle or 110 mg/kg ibalizumab-uiyk every week from Gestation Day 20-22 (GD 20-22) until parturition on GD 160 ± 10. Significant changes in infant monkey immune cell levels on Postnatal Day (PND) 14 (mean decreases of 78% in CD4+ T cells and 46% in B cells and increases of 2.3-fold in CD8+ T cells) and PND 28 (mean decreases of 73% in CD4+ T cells and increases of 2.2-fold in CD8+ T cells), attributed to in utero ibalizumab-uiyk exposure, were observed relative to concurrent controls. The lymphocyte changes correlated with infant ibalizumab-uiyk serum concentrations and appeared to return to near normal levels between PND 28-91, when ibalizumab-uiyk concentrations were nearly undetectable. Although ibalizumab-uiyk exposure in these infant monkeys may be significantly higher than in human infants following in utero exposure at the recommended human maintenance dose, the risk of ibalizumab-uiyk-induced immunosuppression in human infants is possible. No meaningful differences in infant monkey lymphocyte counts were observed on PND 180. Further, no differences in immune cell function were observed in a T cell-dependent response assay conducted on PND 138 to 180 ± 2 following immunization of the infant monkeys with keyhole limpet hemocyanin. One treatment-group infant monkey died on PND 24 from a systemic viral infection with secondary superficial bacterial infection which was acquired during the postnatal period. Despite the low incidence (1 of 20 infants), the death may be related to ibalizumab-uiyk-induced immunosuppression. Decreases in CD4+ T cells (93%), and B cells (92%) were observed in this infant on PND 14, and decreased cellularity was observed in the spleen, thymus and mandibular lymph node. Unlike the rest of the ibalizumab-exposed infant monkey population, this infant also exhibited a decrease in CD8+ T cells of 71% on PND 14. Body weight was also decreased in this infant between PND 14 and 24. No structural abnormalities were observed among the ibalizumab-uiyk-exposed infants. In addition, no maternal toxicities, including no changes in maternal lymphocyte subsets or effects on embryo-fetal survival, were observed.

8.2 Lactation

Risk Summary
The Centers for Disease Control and Prevention recommend that HIV-1-infected mothers in the United States not breastfeed their infants to avoid the risk of postnatal transmission of HIV-1 infection.

No data are available regarding the presence of TROGARZO in human milk, the effects on the breastfed child, or the effects on milk production. Human IgG is present in human milk, although published data indicate that antibodies in breast milk do not enter the neonatal or infant circulation system in substantial amounts. Because of the potential for HIV-1 transmission, instruct mothers not to breastfeed if they are receiving TROGARZO.

8.4 Pediatric Use

The safety and effectiveness of TROGARZO in pediatric patients have not been established.

8.5 Geriatric Use

No studies have been conducted with TROGARZO in geriatric patients.

11 DESCRIPTION

TROGARZO is a CD4-directed post-attachment HIV-1 inhibitor.

Ibalizumab-uiyk is a CD4 domain 2-directed humanized monoclonal antibody of immunoglobulin G (IgG) isotype 4 with a molecular weight of approximately 150 kDa. Ibalizumab-uiyk is produced by recombinant DNA technology in murine myeloma non-secreting 0 (NS0) cells.

TROGARZO Injection is a sterile, colorless to slightly yellow and clear to slightly opalescent solution with no visible particles in a single-dose vial for intravenous administration (by IV infusion or IV push). Each single-dose vial delivers approximately 1.33 mL containing 200 mg of ibalizumab-uiyk, and contains the following inactive ingredients: 10 mM L-histidine (2.06 mg), 0.045% polysorbate 80 (0.60 mg), 52 mM sodium chloride (4.04 mg) and 5.2% sucrose (69.2 mg). TROGARZO solution has a pH of 6.0 and contains no preservative.

12 CLINICAL PHARMACOLOGY

12.1 Mechanism of Action

Ibalizumab-uiyk is an HIV-1 antiretroviral drug [see Microbiology (12.4)].

12.2 Pharmacodynamics

A clear trend was identified between exposure and response rate for the Phase 2b trial (TMB-202) which studied two different intravenous doses given at two different dosing intervals (every 4 weeks vs. every 2 weeks). The recommended intravenous dosing regimen consisting of a 2,000 mg loading dose followed by a maintenance dose of 800 mg every 2 weeks was selected on the basis of these results.

12.3 Pharmacokinetics

Ibalizumab-uiyk administered as a single agent exhibits nonlinear pharmacokinetics. Following single-dose administrations of ibalizumab-uiyk as 0.5 to 1.5-hour infusions, the area under the concentration-time curve increased in a greater than dose-proportional manner, clearance decreased from 9.54 to 0.36 mL/h/kg and elimination half-life increased from 2.7 to 64 hours as the dose increased from 0.3 to 25 mg/kg. The volume of distribution of ibalizumab-uiyk was approximately that of serum volume, at 4.8 L.

Following the recommended dose regimen (a single loading dose of 2,000 mg followed by a maintenance dose of 800 mg every 2 weeks), ibalizumab-uiyk concentrations reached steady-state levels after the first 800 mg maintenance dose with mean concentrations over 30 mcg/mL throughout the dosing interval. Among HIV-infected subjects, the pharmacokinetic data from Trial TMB-302 demonstrated that ibalizumab-uiyk Ctrough and AUC0-tau values between IV push administration and IV infusion administration for maintenance dose were similar. The Cmax values were 25% higher for IV push compared to the IV infusion administration. The increase in Cmax is not considered clinically relevant.

The initial loading dose of ibalizumab-uiyk as an IV push administration over 90 seconds is predicted to have a similar Cmax and AUC relative to IV infusion administration over 30 minutes.

Specific Populations
A population pharmacokinetic analysis was performed to explore the potential effects of selected covariates (age, body weight, sex, baseline CD4^+ cell count) on ibalizumab-uiyk pharmacokinetics. The result suggests that ibalizumab-uiyk concentration decreases as body weight increases; however, the effect is unlikely to impact virologic outcome and does not warrant a dose adjustment.

Pediatric/Geriatric Patients: Ibalizumab-uiyk pharmacokinetics have not been evaluated in pediatric or geriatric patients [see Use in Specific Populations (8.4, 8.5)].

Renal/Hepatic Impairment: No formal studies were conducted to examine the effects of either renal or hepatic impairment on the pharmacokinetics of ibalizumab-uiyk. Renal impairment is not anticipated to impact the pharmacokinetics of ibalizumab-uiyk.

Drug Interaction studies
No drug interaction studies have been conducted with ibalizumab-uiyk. Based on ibalizumab-uiyk’s mechanism of action and target-mediated drug disposition, drug-drug interactions are not expected.

12.4 Microbiology

Mechanism of Action
Ibalizumab-uiyk, a recombinant humanized monoclonal antibody, blocks HIV-1 from infecting CD4^+ T cells by binding to domain 2 of CD4 and interfering with post-attachment steps required for the entry of HIV-1 virus particles into host cells and preventing the viral transmission that occurs via cell-cell fusion.

Ibalizumab-uiyk Does Not Impact CD4 Function
The binding specificity of ibalizumab-uiyk to domain 2 of CD4 allows ibalizumab-uiyk to block viral entry into host cells without causing immunosuppression. Epitope mapping studies indicate that ibalizumab-uiyk binds to a conformational epitope located primarily in domain 2 of the extracellular portion of the CD4 receptor. This epitope is positioned on the surface of CD4 opposite to the site in domain 1 that is required for CD4 binding of the MHC class II molecules and therefore does not interfere with CD4-mediated immune functions. Additionally, ibalizumab-uiyk does not interfere with gp120 attachment to CD4.

Antiviral Activity
Ibalizumab-uiyk inhibits the replication of CCR5- and CXCR4-tropic laboratory strains and primary isolates of HIV-1 in phytohemagglutinin stimulated peripheral blood lymphocytes. The median EC50 value (50% effective concentration) for ibalizumab-uiyk against HIV-1 group M isolates (subtypes A, B, C, D, E, or O) was 8 ng/mL (n = 15, range of 0.4 to 600 ng/mL) in cell culture, with lower susceptibility observed in macrophage-tropic HIV-1 strains (BaL, JR-CSF, YU2, and ADA-M). In a single-cycle infection assay, ibalizumab-uiyk inhibited 17 clinical isolates of subtype B with a median EC50 value of 12 ng/mL (range of 8.8 to 16.9 ng/mL; mean 12 ± 3 ng/mL) and a median maximum percentage inhibition (MPI) of 97% (range of 89 to 99%; mean 97 ± 3%). Three CCR5-tropic clinical isolates from subtypes B, C, and D, were inhibited with EC50 values ranging from 59-66 ng/mL and 3 CXCR4-tropic clinical isolates from subtypes B, C, and D, with EC50 values ranging from 44-59 ng/mL.

Antiviral Activity in Combination with Other Antiviral Agents
No antagonism was observed when PBMCs or MAGI-CCR5 cells infected with the subtype B Ba-L or ADA variants of HIV-1 were incubated with ibalizumab-uiyk in combination with the CCR5 co-receptor antagonist maraviroc or when PBMCs infected with the subtype B HT/92/599 variant of HIV-1 were incubated with ibalizumab-uiyk in combination with the gp41 fusion inhibitor enfuvirtide; a nonnucleoside reverse transcriptase inhibitor (efavirenz); nucleoside analog reverse transcriptase inhibitors (abacavir, didanosine, emtricitabine, tenofovir, or zidovudine); or a protease inhibitor (atazanavir).

Antiviral Activity in Antiretroviral-Resistant Virus
Subjects enrolled in TMB-301 were heavily treatment-experienced subjects infected with multidrug resistant HIV-1. Ibalizumab-uiyk inhibited 38 baseline isolates at a median EC50 value of 31 ng/mL (range of 13 to 212 ng/mL; mean 39 ± 35 ng/mL) with a median MPI of 97% (range of 41-100%; mean 91 ± 14%). For 10 subjects in TMB-301 who failed treatment, at the time of failure the median ibalizumab-uiyk EC50 value was 566 ng/mL (range of 148 to >54,900 ng/mL; mean 11,768 ± 21,650 ng/mL) representing an EC50 value shift of >18-fold. For the HIV-1 derived from the same subjects, the median MPI was 55% (range of 43-72%; mean 56 ± 8%) representing a 42 percentage point reduction.

Decreased Susceptibility
Decreased susceptibility to ibalizumab-uiyk, as defined by a decrease in MPI, has been observed in some subjects experiencing virologic failure and may be associated with genotypic changes in the HIV-1 envelope coding sequence that results in the loss of potential N-linked glycosylation sites (PNGS) in the V5 loop of gp120. The clinical significance of decreased susceptibility to ibalizumab-uiyk has not been established.

Cross-Resistance
Phenotypic and genotypic test results revealed no evidence of cross-resistance between ibalizumab-uiyk and any of the approved classes of anti-retroviral drugs (CCR5 co-receptor antagonists, gp41 fusion inhibitors, integrase strand transfer inhibitors [INSTIs], non-nucleos(t)ide reverse transcriptase inhibitors [NNRTIs], nucleos(t)ide reverse transcriptase inhibitors [NRTIs], or protease inhibitors [PIs]). Ibalizumab-uiyk is active against HIV-1 resistant to all approved antiretroviral agents and exhibits antiretroviral activity against R5-tropic, X4-tropic, and dual-tropic HIV-1.

Decreased susceptibility to ibalizumab-uiyk following multiple dose administrations of ibalizumab-uiyk has been observed in some subjects. Cell culture studies performed with HIV-1 variants with reduced susceptibility to ibalizumab-uiyk indicate that phenotypic changes associated with resistance to ibalizumab-uiyk do not alter susceptibility to other approved agents and do not result in the selection of CD4-independent viral isolates.

CD4 Polymorphisms and Ibalizumab-uiyk Activity
CD4 polymorphisms reported in public databases were analyzed to determine if any naturally occurring amino acid substitutions in the CD4 molecule from different human populations would potentially impact the antiviral activity of ibalizumab-uiyk. None of the known CD4 polymorphisms are likely to have an impact on ibalizumab-uiyk binding to CD4.

12.6 Immunogenicity

As with all therapeutic proteins, there is potential for immunogenicity. The detection of antibody formation is highly dependent on the sensitivity and specificity of the assay. Additionally, the observed incidence of antibody (including neutralizing antibody) positivity in an assay may be influenced by several factors including assay methodology, sample handling, timing of sample collection, concomitant medications, and underlying disease. For these reasons, comparison of the incidence of antibodies to ibalizumab-uiyk in the studies described below with the incidence of antibodies in other studies or to other products may be misleading.

All subjects enrolled in clinical trial TMB-301 and trial TMB-202 (a Phase 2b clinical trial that studied TROGARZO administered intravenously as 2,000 mg every 4 weeks or 800 mg every 2 weeks; the safety and effectiveness of this dosing regimen has not been established), were tested for the presence of anti-ibalizumab antibodies throughout their participation. One sample tested positive with low titer anti-ibalizumab antibodies. No adverse reaction or reduced efficacy was attributed to the positive sample reported in this subject.

13 NONCLINICAL TOXICOLOGY

13.1 Carcinogenesis, Mutagenesis, Impairment of Fertility

Carcinogenesis, mutagenesis, and fertility studies with ibalizumab-uiyk have not been conducted.

14 CLINICAL STUDIES

Trial TMB-301:
Trial TMB-301 was a single arm, multicenter clinical trial conducted in 40 heavily treatment-experienced HIV-infected subjects with multidrug resistant HIV-1. Subjects were required to have a viral load greater than 1,000 copies/mL and documented resistance to at least one antiretroviral medication from each of three classes of antiretroviral medications as measured by resistance testing. Subjects must have been treated with antiretrovirals for at least 6 months and be failing or had recently failed (i.e., in the last 8 weeks) therapy.

The trial was composed of three discrete periods:

- Control period (Day 0 to Day 6): Subjects were either monitored on their current failing therapy or received no therapy if they had failed and discontinued treatment within the 8 weeks preceding screening. This was an observational period to establish baseline HIV viral load.
- Functional monotherapy period (Day 7 to Day 13): All subjects received a 2,000 mg loading dose of TROGARZO on Day 7. Subjects on a failing ART regimen continued to receive their failing regimen in addition to the loading dose of TROGARZO. This period was to establish the virologic activity of TROGARZO.
- Maintenance period (Day 14 to Week 25): On Day 14 of the treatment period, viral load was assessed for the primary endpoint, and thereafter the background regimen was optimized to include at least one drug to which the subjects virus was susceptible. The use of an investigational drug(s) as a component of the optimized background regimen was allowed. Beginning at Day 21, an 800 mg maintenance dose of TROGARZO was administered every two weeks through Week 25. This period was to establish the safety and durability of virologic suppression of TROGARZO when used in combination with an optimized background regimen.

The majority of subjects in Trial TMB-301 were male (85%), white (55%) and between 23 and 65 years of age (mean [SD] age: 50.5 [11.0] years). At Baseline, median viral load and CD4^+ T cell counts were 35,350 copies/mL and 73 cells/mm^3, respectively. The subjects were heavily treatment-experienced: 53% of participants had been treated with 10 or more antiretroviral drugs prior to trial enrollment; 98% percent had been treated with NRTIs, 98% with PIs, 80% with NNRTIs, 78% with INSTIs, 30% with gp41 fusion inhibitors, and 20% with CCR5 co-receptor antagonists.

The primary efficacy endpoint was the proportion of subjects achieving a 0.5 log10 decrease in viral load from the beginning to the end of the "Functional monotherapy period" as compared to the proportion of subjects achieving a 0.5 log10 decrease from the beginning to the end of the "Control period", as defined above. The results of the primary endpoint analysis are shown in Table 5 below.

Table 5. Proportion of Subjects Achieving a 0.5 log10 Decrease in Viral Load at the End of the Control and Functional Monotherapy Periods
 | Proportion of Subjects Achieving a 0.5 log10 Decrease in Viral Load N=40 | 95% CI [exact 95% confidence interval. p < 0.0001 based on McNemars test comparing the proportion of subjects achieving 0.5 log10 decrease in viral load at the end of the control and functional monotherapy periods.]
End of Control Period | 3% | (0.06%, 13%)
End of Functional Monotherapy Period | 83% | (67%, 93%)

At Week 25, viral load <50 and <200 HIV-1 RNA copies/mL was achieved in 43% and 50% of subjects, respectively. Fifty-five percent of subjects had a 1 log10 reduction in viral load, and 48% of subjects had a 2 log10 reduction in viral load at Week 25. An increase in the mean and median number of CD4^+ T-cells (44 cells/mm^3 and 17 cells/mm^3, respectively) was observed from Baseline to Week 25. Week 25 outcomes are shown in Table 6 and Table 7.

Table 6. Trial TMB 301 Virologic Outcomes (Snapshot Algorithm) at Week 25
 | TROGARZO (N=40)
HIV RNA < 50 copies/mL at Week 25 HIV RNA 50 copies/mL at Week 25* [included subjects who had ≥ 50 copies/mL in the Week 25 window, subjects who discontinued study drug due to lack of efficacy, and subjects who discontinued study drug for reasons other than an AE, death and at the time of discontinuation had a viral value ≥ 50 copies/mL] | 43% 45%
HIV RNA < 200 copies/mL at Week 25 HIV RNA 200 copies/mL at Week 25 [included subjects who had ≥ 200 copies/mL in the Week 25 window, subjects who discontinued study drug due to lack of efficacy, and subjects who discontinued study drug for reasons other than an AE, death and at the time of discontinuation had a viral value ≥ 200 copies/mL] | 50% 38%
No virologic data at Week 25; Discontinued due to AE or death | 13%

Table 7. Virologic Response at Week 25 by Baseline CD4 Cell count, Viral Load, Integrase Inhibitor Resistance and OSS [OSS Overall Susceptibility Score. The OSS indicates the number of fully active drugs in a subjects OBR based on both current and available historical resistance test results. Demonstrating drug susceptibility by both genotypic and phenotypic testing was required, when testing by both methods was technically feasible. As an example, an OSS of 2 would indicate that the HIV-1 isolate tested was fully susceptible to two drugs in the OBR.]
 | Subjects achieving <50 HIV-1 RNA copies/mL (%) | Subjects achieving <200 HIV-1 RNA copies/mL (%)
CD4 Cell Counts; <50 (n=17); 50-200 (n=10); >200 (n=13) | 18; 60; 62 | 24; 70; 69
Viral Load; 100,000 (n=33); >100,000 (n=7) | 49; 14 | 58; 14
Resistance; With INSTI Resistance (n=27); Without INSTI Resistance (n=13) | 41; 46 | 44; 62
OSS; 0 (n=5); 1 (n=12); 2 (n=18); 3 (n=3); 4 (n=2) | 20; 42; 50; 33; 50 | 20; 50; 61; 33; 50

16 HOW SUPPLIED/STORAGE AND HANDLING

TROGARZO (ibalizumab-uiyk) injection is a sterile colorless to slightly yellow and clear to slightly opalescent solution with no visible particles for intravenous administration (by IV infusion or IV push). It is packaged in a single-dose 2 mL clear glass vial containing 200 mg/1.33 mL (150 mg/mL) of ibalizumab-uiyk. TROGARZO vial stopper is not made with natural rubber latex.

TROGARZO is available in a carton containing two single-dose vials (NDC 62064-122-02).

Store vials under refrigeration at 2 to 8ºC (36-46 ºF). Do not freeze and protect from light.

Once diluted, the TROGARZO solution should be administered immediately [see Dosage and Administration (2.2)].

17 PATIENT COUNSELING INFORMATION

Advise the patient to read the FDA-approved patient labeling (Patient Information).

Hypersensitivity
Advise patients of the risk of hypersensitivity reactions including anaphylaxis. Instruct patients to seek immediate medical attention if signs or symptoms of hypersensitivity occur or are suspected. Advise patients who have had clinically significant hypersensitivity reactions to TROGARZO that they should not receive TROGARZO [see Contraindications (4), Warnings and Precautions (5.1)].

Immune Reconstitution Syndrome
Immune Reconstitution Inflammatory Syndrome: Advise patients that immune reconstitution syndrome has been reported in a patient receiving TROGARZO and to inform their health care provider immediately of any symptoms of infection [see Warnings and Precautions (5.2)].

Important Administration Information
Advise the patient it is important to receive TROGARZO injections every two weeks as recommended by their healthcare professional and not to change the dosing schedule of TROGARZO or any antiretroviral medication without consulting their healthcare provider. Advise the patient to contact their healthcare provider immediately if they stop taking TROGARZO or any other drug in their antiretroviral regimen [see Dosage and Administration (2)]. Advise the patient that they may receive TROGARZO loading dose by IV infusion over at least 30 minutes or by IV push over 90 seconds and they may receive TROGARZO maintenance doses by IV infusion over 15 minutes or IV push over 30 seconds. Also, advise the patient to seek counsel of the healthcare provider regarding the most appropriate route of administration [see Dosage and Administration (2.3)].

Embryo-fetal Toxicity
Advise pregnant individuals and females of reproductive potential of the potential risk of reversible immunosuppression in infants exposed to TROGARZO during pregnancy and to inform their healthcare provider of a known or suspected pregnancy [see Warning and Precautions (5.3) and Use in Specific Populations (8.1)].

Lactation
Instruct women with HIV-1 infection not to breastfeed because HIV-1 can be passed to the baby in breast milk [see Use in Specific Populations (8.2)].

Manufactured by Theratechnologies Inc., 2015 Peel Street, Suite 1100, Montréal, Québec Canada H3A 1T8
US License No. 2091 for Theratechnologies Inc.

PATIENT INFORMATION

TROGARZO® (tro-gar-zo)
(ibalizumab-uiyk)
injection

What is TROGARZO?
TROGARZO is a prescription medicine that is used with other antiretroviral medicines to treat Human Immunodeficiency Virus-1 (HIV-1) infection in adults who:

- have received several anti-HIV-1 regimens in the past, and
- have HIV-1 virus that is resistant to many antiretroviral medicines, and
- who are failing their current antiretroviral therapy

HIV-1 is the virus that causes Acquired Immune Deficiency Syndrome (AIDS).
It is not known if TROGARZO is safe and effective in children.

Do not receive TROGARZO if you have had an allergic reaction to TROGARZO or any of the ingredients in TROGARZO. See the end of this leaflet for a complete list of ingredients in TROGARZO.

Before you receive TROGARZO, tell your healthcare provider about all of your medical conditions, including if you:

- are pregnant or plan to become pregnant. It is not known if TROGARZO may harm your unborn baby. Tell your healthcare provider if you become pregnant during treatment with TROGARZO. Pregnancy Registry: There is a pregnancy registry for women who take antiretroviral medicines during pregnancy. The purpose of this registry is to collect information about the health of you and your baby. Talk with your healthcare provider about how you can take part in this registry.

- are breastfeeding or plan to breastfeed. Do not breastfeed if you are receiving TROGARZO.
  - You should not breastfeed if you have HIV-1 because of the risk of passing HIV-1 to your baby.
  - It is not known if TROGARZO passes into breast milk.
    Talk with your healthcare provider about the best way to feed your baby during treatment with TROGARZO.

Tell your healthcare provider about all the medicines you take, including prescription and over-the-counter medicines, vitamins, and herbal supplements.

How will I receive TROGARZO?

- You will receive TROGARZO by your healthcare provider as an intravenous infusion (IV infusion) or as an intravenous push (IV push). The first dose will be given over 30 minutes by IV infusion or 90 seconds by IV push. After the first dose, the dose will be given over 15 minutes by IV infusion or 30 seconds by IV push. A healthcare provider will monitor you during the TROGARZO IV infusion or IV push and for a period of time after your IV infusion or IV push.
- You will receive TROGARZO every two weeks.
- It is important that you receive TROGARZO every two weeks as instructed by your healthcare provider. Do not change the schedule of your TROGARZO IV infusion or IV push, or any of your antiretroviral medicines without talking to your healthcare provider first.
- Tell your healthcare provider right away if you stop receiving TROGARZO or stop taking any other antiretroviral medicines.

What are the possible side effects of TROGARZO?
TROGARZO can cause serious side effects, including:

- Allergic reactions. TROGARZO can cause allergic reactions, including serious reactions, during and after IV infusion or IV push. Tell your healthcare provider or nurse, or get medical help right away if you get any of the following symptoms of an allergic reaction:

o trouble breathing
o cough
o swelling in your throat
o hot flush
o wheezing
o nausea
o chest pain
o vomiting
o chest tightness

- Changes in your immune system (Immune Reconstitution Inflammatory Syndrome) can happen when you start taking HIV-1 medicines. Your immune system might get stronger and begin to fight infections that have been hidden in your body for a long time. Tell your healthcare provider right away if you start having new symptoms after receiving TROGARZO.
  The most common side effects of TROGARZO include:
  - diarrhea
  - nausea
  - dizziness
  - rash

These are not all of the possible side effects of TROGARZO.

Call your doctor for medical advice about side effects. You may report side effects to FDA at 1-800-FDA-1088.

You may also report side effects to at 1-833-23THERA (1-833-238-4372).

General information about the safe and effective use of TROGARZO.

Medicines are sometimes prescribed for purposes other than those listed in a Patient Information leaflet. You can ask your healthcare provider for information about TROGARZO that is written for health professionals.

What are the ingredients in TROGARZO?
Active ingredient: ibalizumab-uiyk
Inactive ingredients: L-histidine, polysorbate 80, sodium chloride, and sucrose.

TROGARZO does not contain any preservative. TROGARZO vial stopper is not made with natural rubber latex.

Manufactured by Theratechnologies Inc., 2015 Peel Street, Suite 1100, Montréal, Québec Canada H3A 1T8
US License No. 2091 for Theratechnologies Inc.

For more information, call 1-833-23THERA (1-833-238-4372) or go to www.TROGARZO.com.

This Patient Information has been approved by the U.S. Food and Drug Administration. Revised: 12/2023

Principal Display Panel - Trogarzo Vial Label

Rx only
Trogarzo®

(ibalizumab-uiyk) Injection

200 mg/1.33 mL (150 mg/mL)

For Intravenous Use Only.

Single-dose vial.

Discard unused portion.

Store at 2º to 8ºC (36º-46 ºF)
Do not freeze.
Protect from light.

Dosage: See prescribing information.

Principal Display Panel - Trogarzo Carton Label

Package contains two vials.

Single-dose vial.

NDC 62064-122-02

Rx only

Trogarzo®

(ibalizumab-uiyk)
Injection

200 mg/1.33 mL (150 mg/mL)

For Intravenous Use Only.

Single-dose vial. Discard unused portion.

Manufactured by: Theratechnologies Inc.
2015 Peel Street, Suite 1100,
Montréal, Québec Canada H3A 1T8